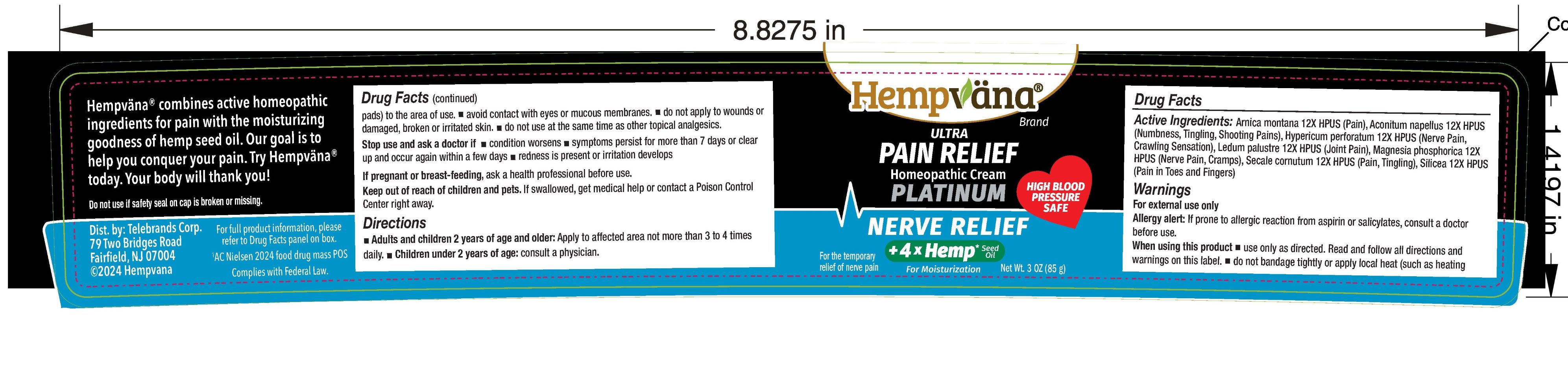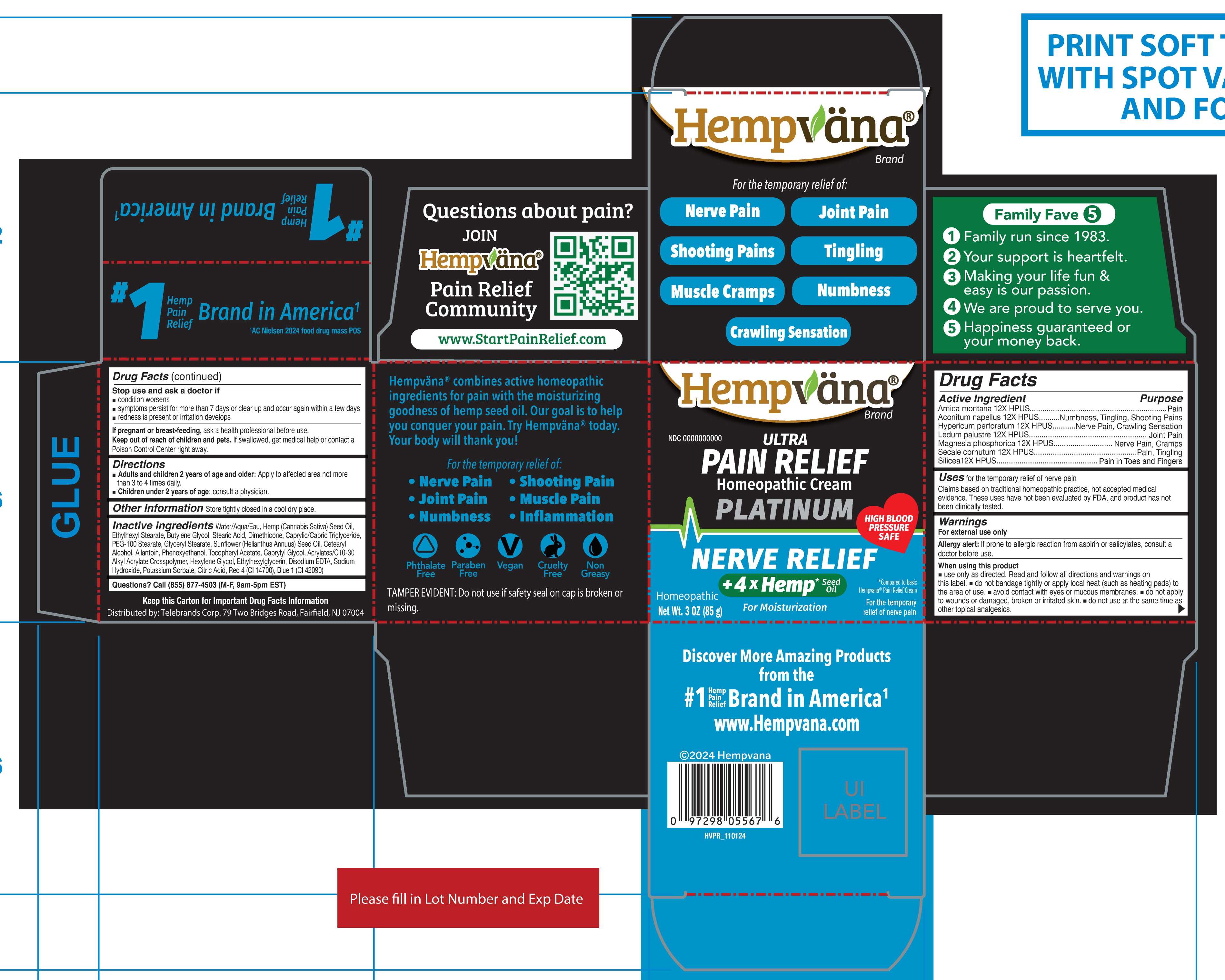 DRUG LABEL: Hempvana Ultra Pain Relief Homeopathic Cream Platinum - Nerve Relief
NDC: 73287-041 | Form: CREAM
Manufacturer: TELEBRANDS CORP
Category: homeopathic | Type: HUMAN OTC DRUG LABEL
Date: 20241121

ACTIVE INGREDIENTS: ACONITUM NAPELLUS 12 [hp_X]/85 g; ARNICA MONTANA 12 [hp_X]/85 g; HYPERICUM PERFORATUM 12 [hp_X]/85 g; LEDUM PALUSTRE WHOLE 12 [hp_X]/85 g; CLAVICEPS PURPUREA SCLEROTIUM 12 [hp_X]/85 g; SILICON DIOXIDE 12 [hp_X]/85 g; MAGNESIUM PHOSPHATE, DIBASIC TRIHYDRATE 12 [hp_X]/85 g
INACTIVE INGREDIENTS: CANNABIS SATIVA SEED OIL; CETOSTEARYL ALCOHOL; ALLANTOIN; PHENOXYETHANOL; CAPRYLYL GLYCOL; CARBOMER INTERPOLYMER TYPE A (ALLYL SUCROSE CROSSLINKED); ETHYLHEXYLGLYCERIN; EDETATE DISODIUM ANHYDROUS; CITRIC ACID MONOHYDRATE; FD&C BLUE NO. 1; BUTYLENE GLYCOL; DIMETHICONE; GLYCERYL MONOSTEARATE; STEARIC ACID; PEG-100 STEARATE; SODIUM HYDROXIDE; POTASSIUM SORBATE; WATER; .ALPHA.-TOCOPHEROL ACETATE; HEXYLENE GLYCOL; SUNFLOWER OIL; FD&C RED NO. 4; ETHYLHEXYL STEARATE; MEDIUM-CHAIN TRIGLYCERIDES

Hempvana Ultra Pain Relief Homeopathic Cream Platinum - Nerve Relief

Active ingredients

Arnica montana 12X HPUS

Aconitum napellus 12X HPUS

Hypericum perforatum 12X HPUS

Ledum palustre 12X HPUS

Magnesia phosphorica 12X HPUS

Secale cornutum 12X HPUS

Silicea 12X HPUS

Purpose

Arnica montana 12X HPUS............................Pain

Aconitum napellus 12X HPUS........................Numbness, Tingling, Shooting Pains

Hypericum perforatum 12X HPUS..................Nerve Pain, Crawling Sensation

Ledum palustre 12X HPUS.............................Joint Pain

Magnesia phosphorica 12X HPUS..................Nerve Pain, Cramps

Secale cornutum 12X HPUS...........................Pain, Tingling

Silicea 12X HPUS............................................Pain in Toes and Fingers

Uses

for the temporary relief of nerve pain

Claims based on traditional homeopathic practice, not accepted medical evidence. These uses have not been evaluated by FDA, and product has not been clinically tested.

Warnings

For external use only

Allergy alert:If prone to allergic reaction from aspirin or salicylates, consult a doctor before use.

When using this product

- use only as directed. Read and follow all directions and warnings on this label.
- do not bandage tightly or apply local heat (such as heating pads) to the area of use.
- avoid contact with eyes or mucous membranes.
- do not apply to wounds or damaged, broken or irritated skin.
- do not use at the same time as other topical analgesics.

Stop use and ask a doctor if

- condition worsens
- symptoms persist for more than 7 days or clear up and occur again within a few days
- redness is prsent or irritation develops

PREGNANCY OR BREAST FEEDING

If pregnant or breast-feeding,ask a health professional before use.

Keep out of reach of children and pets.If swallowed, get medical help or contact a Poison Control Center right away.

Directions

- Adults and children 2 years of age and older:Apply to affected area not more than 3 to 4 times daily.
- Children under 2 years of age:consult a physician.

Other information

Store tightly closed in a cool dry place.

Inactive ingredients

Water/Aqua/Eau, Ethylhexyl Stearate, Butylene Glycol, Stearic Acid, Dimethicone, Caprylic/Capric Trigylceride, PEG-100 Stearate, Glyceryl Stearate, Cannabis Sativa (Hemp) Seed Oil, Helianthus Annuus (Sunflower) Seed Oil, Cetearyl Alcohol, Allantoin, Phenoxyethanol, Tocopheryl Acetate, Caprylyl Glycol, Acrylates/C10-30 Alkyl Acrylate Crosspolymer, Hexylene Glycol, Ethylhexylglycerin, Disodium EDTA, Sodium Hydroxide, Potassium Sorbate, Citric Acid, Red 4 (CI 14700), Blue 1 (CI 42090)

Questions?

Call (855) 877-4503 (M-F, 9am-5pm EST)

PACKAGE LABEL

Hempvana Brand

NDC 73287-019-01

Ultra Pain Relief Homeopathic Cream

Platinum

Nerve Relief

+4xHemp Seed Oil

For Moisturization

For the temporary relief of nerve pain

Net Wt. 3 OZ (85 g)